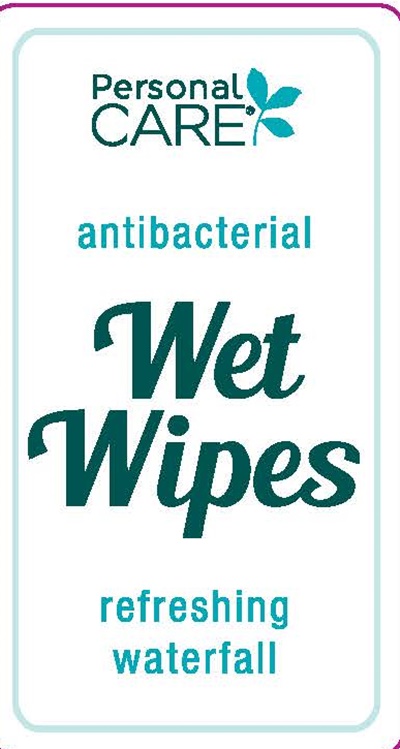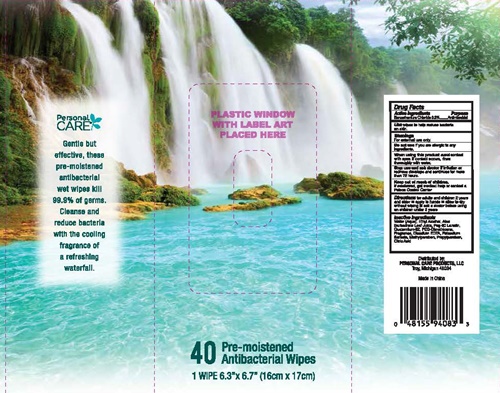 DRUG LABEL: Wet Wipes
                        
NDC: 29500-0908 | Form: CLOTH
Manufacturer: Personal Care Products
Category: otc | Type: HUMAN OTC DRUG LABEL
Date: 20180502

ACTIVE INGREDIENTS: BENZETHONIUM CHLORIDE .009 g/3 g
INACTIVE INGREDIENTS: WATER; ALCOHOL; ALOE VERA LEAF; PEG-60 LANOLIN; QUATERNIUM-52; DIMETHICONE; EDETATE DISODIUM; POTASSIUM SORBATE; METHYLPARABEN; PROPYLPARABEN; CITRIC ACID MONOHYDRATE

Wet Wipes - 0908

Drug Facts Active ingredients

Benzethonium Chloride 0.3%

Purpose

Antimicrobial

Keep out of reach of children.

If swallowed, get medical help or contact a Poison Control Center.

Use

wipes to help reduce bacteria on the skin.

Warnings

For external use only.

Flammable. Keep away from heat and flame.

Do not use in the eyes. In case of contact, rinse eyes thoroughly with water.

Stop use and ask a doctor if irritation or redness develop and persist for more than 72 hours.

Do not use

if you are allergic to any ingredients.

When using this product

avoid contact with eyes. If contact occurs, rinse thoroughly with water.

Stop use and ask a doctor if

irritation or redness develops and continues for more than 72 hours.

Directions

for adults and children 2 years and older

- apply to hands
- allow to dry without wiping
- ask a doctor before using on children under 2 years

Inactive ingredients

Water (Aqus), Ethyl Alcohol, Aloe Barbadnsis Leaf Juice, Peg-60 Lanolin, Quaternium-52, PEG-Dimethicone, Fragrance, Disodium EDTA, Potassium Sorbate, Methylparaben, Propylparaben, Citric Acid

PACKAGE LABEL

Personal Care

antibacterial

Wet Wipes

refreshing waterfall

40 Pre-moistened
Antibacterial Wipes

1 Wipe 6.3" x 6.7" (16cm x 17cm)

Gentle but effective, these pre-moistened antibacterial wet wipes kill 99.9% of germs.
Cleanse and reduce bacteria with the cooling fragrance of a refreshing waterfall.

Distributed by:
PERSONAL CARE PRODUCTS, LLC
Troy, Michigan 48084

Made in China